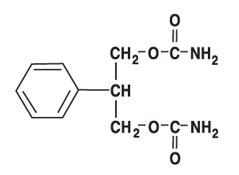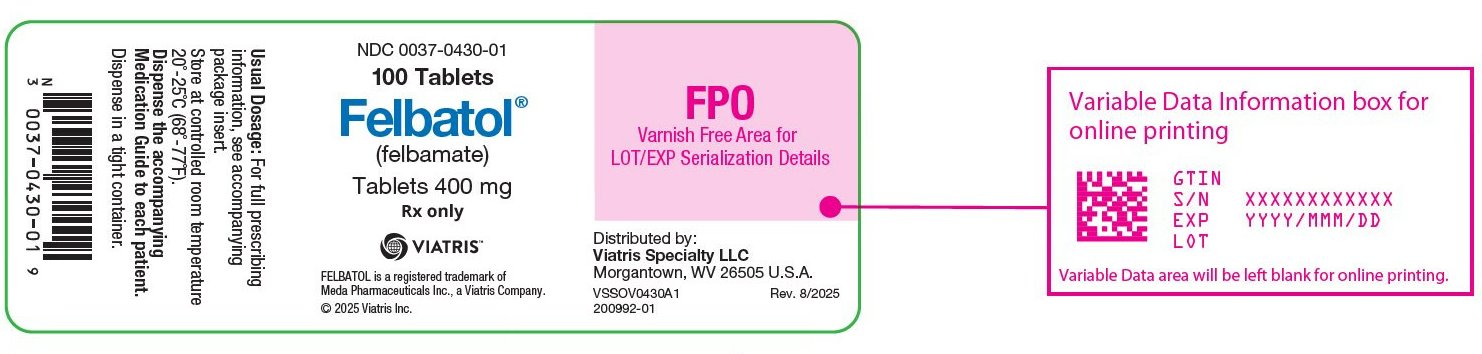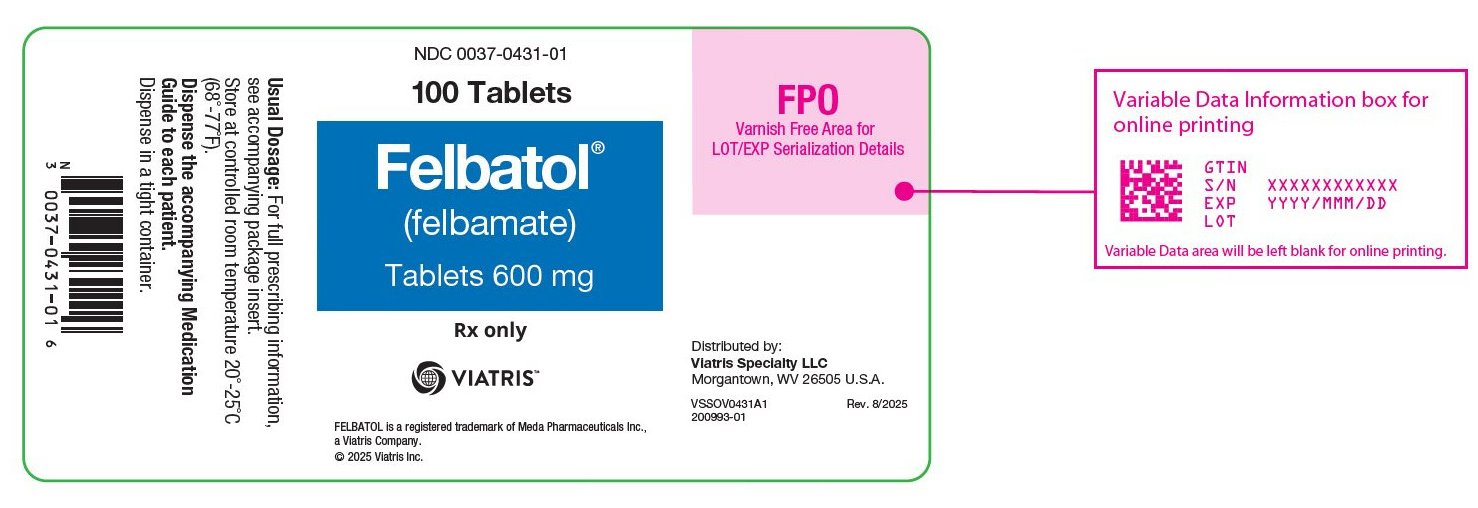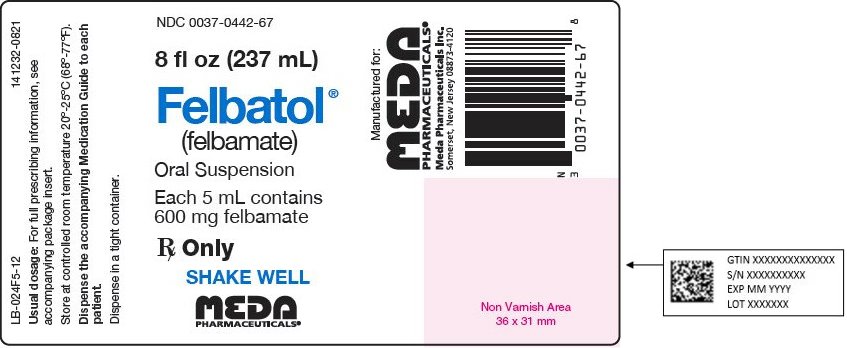 DRUG LABEL: Felbatol
NDC: 0037-0430 | Form: TABLET
Manufacturer: Viatris Specialty LLC
Category: prescription | Type: HUMAN PRESCRIPTION DRUG LABEL
Date: 20250815

ACTIVE INGREDIENTS: FELBAMATE 400 mg/1 1

Before Prescribing Felbatol® (felbamate), the physician should be thoroughly familiar with the details of this prescribing information.
FELBATOL® SHOULD NOT BE USED BY PATIENTS UNTIL THERE HAS BEEN A COMPLETE DISCUSSION OF THE RISKS AND THE PATIENT, PARENT, OR GUARDIAN HAS BEEN PROVIDED THE FELBATOL WRITTEN ACKNOWLEDGEMENT (SEE PATIENT/PHYSICIAN ACKNOWLEDGMENT FORM).

WARNING

1. APLASTIC ANEMIA

THE USE OF FELBATOL® (felbamate) IS ASSOCIATED WITH A MARKED INCREASE IN THE INCIDENCE OF APLASTIC ANEMIA. ACCORDINGLY, FELBATOL® SHOULD ONLY BE USED IN PATIENTS WHOSE EPILEPSY IS SO SEVERE THAT THE RISK OF APLASTIC ANEMIA IS DEEMED ACCEPTABLE IN LIGHT OF THE BENEFITS CONFERRED BY ITS USE (SEE INDICATIONS). ORDINARILY, A PATIENT SHOULD NOT BE PLACED ON AND/OR CONTINUED ON FELBATOL® WITHOUT CONSIDERATION OF APPROPRIATE EXPERT HEMATOLOGIC CONSULTATION.

AMONG FELBATOL® TREATED PATIENTS, APLASTIC ANEMIA (PANCYTOPENIA IN THE PRESENCE OF A BONE MARROW LARGELY DEPLETED OF HEMATOPOIETIC PRECURSORS) OCCURS AT AN INCIDENCE THAT MAY BE MORE THAN A 100 FOLD GREATER THAN THAT SEEN IN THE UNTREATED POPULATION (I.E., 2 TO 5 PER MILLION PERSONS PER YEAR). THE RISK OF DEATH IN PATIENTS WITH APLASTIC ANEMIA GENERALLY VARIES AS A FUNCTION OF ITS SEVERITY AND ETIOLOGY; CURRENT ESTIMATES OF THE OVERALL CASE FATALITY RATE ARE IN THE RANGE OF 20 TO 30%, BUT RATES AS HIGH AS 70% HAVE BEEN REPORTED IN THE PAST.

THERE ARE TOO FEW FELBATOL® ASSOCIATED CASES, AND TOO LITTLE KNOWN ABOUT THEM TO PROVIDE A RELIABLE ESTIMATE OF THE SYNDROME’S INCIDENCE OR ITS CASE FATALITY RATE OR TO IDENTIFY THE FACTORS, IF ANY, THAT MIGHT CONCEIVABLY BE USED TO PREDICT WHO IS AT GREATER OR LESSER RISK.

IN MANAGING PATIENTS ON FELBATOL®, IT SHOULD BE BORNE IN MIND THAT THE CLINICAL MANIFESTATION OF APLASTIC ANEMIA MAY NOT BE SEEN UNTIL AFTER A PATIENT HAS BEEN ON FELBATOL® FOR SEVERAL MONTHS (E.G., ONSET OF APLASTIC ANEMIA AMONG FELBATOL® EXPOSED PATIENTS FOR WHOM DATA ARE AVAILABLE HAS RANGED FROM 5 TO 30 WEEKS). HOWEVER, THE INJURY TO BONE MARROW STEM CELLS THAT IS HELD TO BE ULTIMATELY RESPONSIBLE FOR THE ANEMIA MAY OCCUR WEEKS TO MONTHS EARLIER. ACCORDINGLY, PATIENTS WHO ARE DISCONTINUED FROM FELBATOL® REMAIN AT RISK FOR DEVELOPING ANEMIA FOR A VARIABLE, AND UNKNOWN, PERIOD AFTERWARDS.

IT IS NOT KNOWN WHETHER OR NOT THE RISK OF DEVELOPING APLASTIC ANEMIA CHANGES WITH DURATION OF EXPOSURE. CONSEQUENTLY, IT IS NOT SAFE TO ASSUME THAT A PATIENT WHO HAS BEEN ON FELBATOL® WITHOUT SIGNS OF HEMATOLOGIC ABNORMALITY FOR LONG PERIODS OF TIME IS WITHOUT RISK.

IT IS NOT KNOWN WHETHER OR NOT THE DOSE OF FELBATOL® AFFECTS THE INCIDENCE OF APLASTIC ANEMIA.

IT IS NOT KNOWN WHETHER OR NOT CONCOMITANT USE OF ANTIEPILEPTIC DRUGS AND/OR OTHER DRUGS AFFECTS THE INCIDENCE OF APLASTIC ANEMIA.

APLASTIC ANEMIA TYPICALLY DEVELOPS WITHOUT PREMONITORY CLINICAL OR LABORATORY SIGNS, THE FULL BLOWN SYNDROME PRESENTING WITH SIGNS OF INFECTION, BLEEDING, OR ANEMIA. ACCORDINGLY, ROUTINE BLOOD TESTING CANNOT BE RELIABLY USED TO REDUCE THE INCIDENCE OF APLASTIC ANEMIA, BUT, IT WILL, IN SOME CASES, ALLOW THE DETECTION OF THE HEMATOLOGIC CHANGES BEFORE THE SYNDROME DECLARES ITSELF CLINICALLY. FELBATOL® SHOULD BE DISCONTINUED IF ANY EVIDENCE OF BONE MARROW DEPRESSION OCCURS.

2. HEPATIC FAILURE

EVALUATION OF POSTMARKETING EXPERIENCE SUGGESTS THAT ACUTE LIVER FAILURE IS ASSOCIATED WITH THE USE OF FELBATOL®. THE REPORTED RATE IN THE U.S. HAS BEEN ABOUT 6 CASES OF LIVER FAILURE LEADING TO DEATH OR TRANSPLANT PER 75,000 PATIENT YEARS OF USE. THIS RATE IS AN UNDERESTIMATE BECAUSE OF UNDER REPORTING, AND THE TRUE RATE COULD BE CONSIDERABLY GREATER THAN THIS. FOR EXAMPLE, IF THE REPORTING RATE IS 10%, THE TRUE RATE WOULD BE ONE CASE PER 1,250 PATIENT YEARS OF USE.

OF THE CASES REPORTED, ABOUT 67% RESULTED IN DEATH OR LIVER TRANSPLANTATION, USUALLY WITHIN 5 WEEKS OF THE ONSET OF SIGNS AND SYMPTOMS OF LIVER FAILURE. THE EARLIEST ONSET OF SEVERE HEPATIC DYSFUNCTION FOLLOWED SUBSEQUENTLY BY LIVER FAILURE WAS 3 WEEKS AFTER INITIATION OF FELBATOL®. ALTHOUGH SOME REPORTS DESCRIBED DARK URINE AND NONSPECIFIC PRODROMAL SYMPTOMS (E.G., ANOREXIA, MALAISE, AND GASTROINTESTINAL SYMPTOMS), IN OTHER REPORTS IT WAS NOT CLEAR IF ANY PRODROMAL SYMPTOMS PRECEDED THE ONSET OF JAUNDICE.

IT IS NOT KNOWN WHETHER OR NOT THE RISK OF DEVELOPING HEPATIC FAILURE CHANGES WITH DURATION OF EXPOSURE.

IT IS NOT KNOWN WHETHER OR NOT THE DOSAGE OF FELBATOL® AFFECTS THE INCIDENCE OF HEPATIC FAILURE.

IT IS NOT KNOWN WHETHER CONCOMITANT USE OF OTHER ANTIEPILEPTIC DRUGS AND/OR OTHER DRUGS AFFECT THE INCIDENCE OF HEPATIC FAILURE.

FELBATOL® SHOULD NOT BE PRESCRIBED FOR ANYONE WITH A HISTORY OF HEPATIC DYSFUNCTION.

TREATMENT WITH FELBATOL® SHOULD BE INITIATED ONLY IN INDIVIDUALS WITHOUT ACTIVE LIVER DISEASE AND WITH NORMAL BASELINE SERUM TRANSAMINASES. IT HAS NOT BEEN PROVED THAT PERIODIC SERUM TRANSAMINASE TESTING WILL PREVENT SERIOUS INJURY BUT IT IS GENERALLY BELIEVED THAT EARLY DETECTION OF DRUG-INDUCED HEPATIC INJURY ALONG WITH IMMEDIATE WITHDRAWAL OF THE SUSPECT DRUG ENHANCES THE LIKELIHOOD FOR RECOVERY. THERE IS NO INFORMATION AVAILABLE THAT DOCUMENTS HOW RAPIDLY PATIENTS CAN PROGRESS FROM NORMAL LIVER FUNCTION TO LIVER FAILURE, BUT OTHER DRUGS KNOWN TO BE HEPATOTOXINS CAN CAUSE LIVER FAILURE RAPIDLY (E.G., FROM NORMAL ENZYMES TO LIVER FAILURE IN 2-4 WEEKS). ACCORDINGLY, MONITORING OF SERUM TRANSAMINASE LEVELS (AST AND ALT) IS RECOMMENDED AT BASELINE AND PERIODICALLY THEREAFTER. WHILE THE MORE FREQUENT THE MONITORING THE GREATER THE CHANCES OF EARLY DETECTION, THE PRECISE SCHEDULE FOR MONITORING IS A MATTER OF CLINICAL JUDGEMENT.

FELBATOL® SHOULD BE DISCONTINUED IF EITHER SERUM AST OR SERUM ALT LEVELS BECOME INCREASED ≥ 2 TIMES THE UPPER LIMIT OF NORMAL, OR IF CLINICAL SIGNS AND SYMPTOMS SUGGEST LIVER FAILURE (SEE PRECAUTIONS). PATIENTS WHO DEVELOP EVIDENCE OF HEPATOCELLULAR INJURY WHILE ON FELBATOL® AND ARE WITHDRAWN FROM THE DRUG FOR ANY REASON SHOULD BE PRESUMED TO BE AT INCREASED RISK FOR LIVER INJURY IF FELBATOL® IS REINTRODUCED. ACCORDINGLY, SUCH PATIENTS SHOULD NOT BE CONSIDERED FOR RE-TREATMENT.

DESCRIPTION

Felbatol® (felbamate) is an antiepileptic available as 400 mg and 600 mg tablets and as a 600 mg/5 mL suspension for oral administration. Its chemical name is 2-phenyl-1,3-propanediol dicarbamate.

Felbamate is a white to off-white crystalline powder with a characteristic odor. It is very slightly soluble in water, slightly soluble in ethanol, sparingly soluble in methanol, and freely soluble in dimethyl sulfoxide. The molecular weight is 238.24; felbamate’s molecular formula is C11H14N2O4; its structural formula is:

The inactive ingredients for Felbatol® (felbamate) Tablets 400 mg and 600 mg are starch, microcrystalline cellulose, croscarmellose sodium, lactose, magnesium stearate, FD&C Yellow No. 6, D&C Yellow No. 10, and FD&C Red No. 40 (600 mg tablets only). The inactive ingredients for Felbatol® (felbamate) Oral Suspension 600 mg/5 mL are sorbitol, glycerin, microcrystalline cellulose, carboxymethylcellulose sodium, simethicone, polysorbate 80, methylparaben, saccharin sodium, propylparaben, FD&C Yellow No. 6, FD&C Red No. 40, flavorings, and purified water.

CLINICAL PHARMACOLOGY

Mechanism of Action

The mechanism by which felbamate exerts its anticonvulsant activity is unknown, but in animal test systems designed to detect anticonvulsant activity, felbamate has properties in common with other marketed anticonvulsants. Felbamate is effective in mice and rats in the maximal electroshock test, the subcutaneous pentylenetetrazol seizure test, and the subcutaneous picrotoxin seizure test. Felbamate also exhibits anticonvulsant activity against seizures induced by intracerebroventricular administration of glutamate in rats and N-methyl-D,L-aspartic acid in mice. Protection against maximal electroshock-induced seizures suggests that felbamate may reduce seizure spread, an effect possibly predictive of efficacy in generalized tonic-clonic or partial seizures. Protection against pentylenetetrazol-induced seizures suggests that felbamate may increase seizure threshold, an effect considered to be predictive of potential efficacy in absence seizures.

Receptor-binding studies in vitro indicate that felbamate has weak inhibitory effects on GABA-receptor binding, benzodiazepine receptor binding, and is devoid of activity at the MK-801 receptor binding site of the NMDA receptor-ionophore complex. However, felbamate does interact as an antagonist at the strychnine-insensitive glycine recognition site of the NMDA receptor-ionophore complex. Felbamate is not effective in protecting chick embryo retina tissue against the neurotoxic effects of the excitatory amino acid agonists NMDA, kainate, or quisqualate in vitro. The monocarbamate, p-hydroxy, and 2-hydroxy metabolites were inactive in the maximal electroshock-induced seizure test in mice.

The monocarbamate and p-hydroxy metabolites had only weak (0.2 to 0.6) activity compared with felbamate in the subcutaneous pentylenetetrazol seizure test. These metabolites did not contribute significantly to the anticonvulsant action of felbamate.

Pharmacokinetics

The numbers in the pharmacokinetic section are mean ± standard deviation. Felbamate is well-absorbed after oral administration. Over 90% of the radioactivity after a dose of 1000 mg ^14C felbamate was found in the urine. Absolute bioavailability (oral vs. parenteral) has not been measured. The tablet and suspension were each shown to be bioequivalent to the capsule used in clinical trials, and pharmacokinetic parameters of the tablet and suspension are similar. There was no effect of food on absorption of the tablet; the effect of food on absorption of the suspension has not been evaluated.

Following oral administration, felbamate is the predominant plasma species (about 90% of plasma radioactivity). About 40-50% of absorbed dose appears unchanged in urine, and an additional 40% is present as unidentified metabolites and conjugates. About 15% is present as parahydroxyfelbamate, 2-hydroxyfelbamate, and felbamate monocarbamate, none of which have significant anticonvulsant activity.

Binding of felbamate to human plasma protein was independent of felbamate concentrations between 10 and 310 micrograms/mL. Binding ranged from 22% to 25%, mostly to albumin, and was dependent on the albumin concentration.

Felbamate is excreted with a terminal half-life of 20-23 hours, which is unaltered after multiple doses. Clearance after a single 1200 mg dose is 26±3 mL/hr/kg, and after multiple daily doses of 3600 mg is 30±8 mL/hr/kg. The apparent volume of distribution was 756±82 mL/kg after a 1200 mg dose. Felbamate Cmax and AUC are proportionate to dose after single and multiple doses over a range of 100-800 mg single doses and 1200-3600 mg daily doses. Cmin (trough) blood levels are also dose proportional. Multiple daily doses of 1200, 2400, and 3600 mg gave Cmin values of 30±5, 55±8, and 83±21 micrograms/mL (N=10 patients). Linear and dose proportional pharmacokinetics were also observed at doses above 3600 mg/day up to the maximum dose studied of 6000 mg/day. Felbamate gave dose proportional steady-state peak plasma concentrations in children age 4-12 over a range of 15, 30, and 45 mg/kg/day with peak concentrations of 17, 32, and 49 micrograms/mL.

The effects of race and gender on felbamate pharmacokinetics have not been systematically evaluated, but plasma concentrations in males (N=5) and females (N=4) given felbamate have been similar. The effects of felbamate kinetics on hepatic functional impairment have not been evaluated.

Renal Impairment

Felbamate’s single dose monotherapy pharmacokinetic parameters were evaluated in 12 otherwise healthy individuals with renal impairment. There was a 40-50% reduction in total body clearance and 9-15 hours prolongation of half-life in renally impaired subjects compared to that in subjects with normal renal function. Reduced felbamate clearance and a longer half-life were associated with diminishing renal function.

Pharmacodynamics

Typical Physiologic Responses

1. Cardiovascular

In adults, there is no effect of felbamate on blood pressure. Small but statistically significant mean increases in heart rate were seen during adjunctive therapy and monotherapy; however, these mean increases of up to 5 bpm were not clinically significant. In children, no clinically relevant changes in blood pressure or heart rate were seen during adjunctive therapy or monotherapy with felbamate.

2. Other Physiologic Effects

The only other change in vital signs was a mean decrease of approximately 1 respiration per minute in respiratory rate during adjunctive therapy in children. In adults, statistically significant mean reductions in body weight were observed during felbamate monotherapy and adjunctive therapy. In children, there were mean decreases in body weight during adjunctive therapy and monotherapy; however, these mean changes were not statistically significant. These mean reductions in adults and children were approximately 5% of the mean weights at baseline.

CLINICAL STUDIES

The results of controlled clinical trials established the efficacy of Felbatol® (felbamate) as monotherapy and adjunctive therapy in adults with partial-onset seizures with or without secondary generalization and in partial and generalized seizures associated with Lennox-Gastaut syndrome in children.

Felbatol® Monotherapy Trials in Adults

Felbatol® (3600 mg/day given QID) and low-dose valproate (15 mg/kg/day) were compared as monotherapy during a 112-day treatment period in a multicenter and a single-center double-blind efficacy trial. Both trials were conducted according to an identical study design. During a 56-day baseline period, all patients had at least four partial-onset seizures per 28 days and were receiving one antiepileptic drug at a therapeutic level, the most common being carbamazepine. In the multicenter trial, baseline seizure frequencies were 12.4 per 28 days in the Felbatol® group and 21.3 per 28 days in the low-dose valproate group. In the single-center trial, baseline seizure frequencies were 18.1 per 28 days in the Felbatol® group and 15.9 per 28 days in the low-dose valproate group. Patients were converted to monotherapy with Felbatol® or low-dose valproic acid during the first 28 days of the 112-day treatment period. Study endpoints were completion of 112 study days or fulfilling an escape criterion. Criteria for escape relative to baseline were: (1) twofold increase in monthly seizure frequency, (2) twofold increase in highest 2-day seizure frequency, (3) single generalized tonic-clonic seizure (GTC) if none occurred during baseline, or (4) significant prolongation of GTCs. The primary efficacy variable was the number of patients in each treatment group who met escape criteria.

In the multicenter trial, the percentage of patients who met escape criteria was 40% (18/45) in the Felbatol® group and 78% (39/50) in the low-dose valproate group. In the single-center trial, the percentage of patients who met escape criteria was 14% (3/21) in the Felbatol® group and 90% (19/21) in the low-dose valproate group. In both trials, the difference in the percentage of patients meeting escape criteria was statistically significant (P<.001) in favor of Felbatol®. These two studies by design were intended to demonstrate the effectiveness of Felbatol® monotherapy. The studies were not designed or intended to demonstrate comparative efficacy of the two drugs. For example, valproate was not used at the maximally effective dose.

Felbatol® Adjunctive Therapy Trials in Adults

A double-blind, placebo-controlled crossover trial consisted of two 10-week outpatient treatment periods. Patients with refractory partial-onset seizures who were receiving phenytoin and carbamazepine at therapeutic levels were administered Felbatol® (felbamate) as add-on therapy at a starting dosage of 1400 mg/day in three divided doses, which was increased to 2600 mg/day in three divided doses. Among the 56 patients who completed the study, the baseline seizure frequency was 20 per month. Patients treated with Felbatol® had fewer seizures than patients treated with placebo for each treatment sequence. There was a 23% (P=.018) difference in percentage seizure frequency reduction in favor of Felbatol®.

Felbatol® 3600 mg/day given QID and placebo were compared in a 28-day double-blind add-on trial in patients who had their standard antiepileptic drugs reduced while undergoing evaluations for surgery of intractable epilepsy. All patients had confirmed partial-onset seizures with or without generalization, seizure frequency during surgical evaluation not exceeding an average of four partial seizures per day or more than one generalized seizure per day, and a minimum average of one partial or generalized tonic-clonic seizure per day for the last 3 days of the surgical evaluation. The primary efficacy variable was time to fourth seizure after randomization to treatment with Felbatol® or placebo. Thirteen (46%) of 28 patients in the Felbatol® group versus 29 (88%) of 33 patients in the placebo group experienced a fourth seizure. The median times to fourth seizure were greater than 28 days in the Felbatol® group and 5 days in the placebo group. The difference between Felbatol® and placebo in time to fourth seizure was statistically significant (P=.002) in favor of Felbatol®.

Felbatol® Adjunctive Therapy Trial in Children with Lennox-Gastaut Syndrome

In a 70-day double-blind, placebo-controlled add-on trial in the Lennox-Gastaut syndrome, Felbatol® 45 mg/kg/day given QID was superior to placebo in controlling the multiple seizure types associated with this condition. Patients had at least 90 atonic and/or atypical absence seizures per month while receiving therapeutic dosages of one or two other antiepileptic drugs. Patients had a past history of using an average of eight antiepileptic drugs. The most commonly used antiepileptic drug during the baseline period was valproic acid. The frequency of all types of seizures during the baseline period was 1617 per month in the Felbatol® group and 716 per month in the placebo group. Statistically significant differences in the effect on seizure frequency favored Felbatol® over placebo for total seizures (26% reduction vs. 5% increase, P<.001), atonic seizures (44% reduction vs. 7% reduction, P=.002), and generalized tonic-clonic seizures (40% reduction vs. 12% increase, P=.017). Parent/guardian global evaluations based on impressions of quality of life with respect to alertness, verbal responsiveness, general well-being, and seizure control significantly (P<.001) favored Felbatol® over placebo.

When efficacy was analyzed by gender in four well-controlled trials of felbamate as adjunctive and monotherapy for partial-onset seizures and Lennox-Gastaut syndrome, a similar response was seen in 122 males and 142 females.

INDICATIONS AND USAGE

Felbatol® is not indicated as a first line antiepileptic treatment (see Warnings). Felbatol® is recommended for use only in those patients who respond inadequately to alternative treatments and whose epilepsy is so severe that a substantial risk of aplastic anemia and/or liver failure is deemed acceptable in light of the benefits conferred by its use.

If these criteria are met and the patient has been fully advised of the risk and has provided written acknowledgment, Felbatol® can be considered for either monotherapy or adjunctive therapy in the treatment of partial seizures, with and without generalization, in adults with epilepsy and as adjunctive therapy in the treatment of partial and generalized seizures associated with Lennox-Gastaut syndrome in children.

CONTRAINDICATIONS

Felbatol® is contraindicated in patients with known hypersensitivity to Felbatol®, its ingredients, or known sensitivity to other carbamates. It should not be used in patients with a history of any blood dyscrasia or hepatic dysfunction.

WARNINGS

See Boxed Warning regarding aplastic anemia and hepatic failure.

Antiepileptic drugs should not be suddenly discontinued because of the possibility of increasing seizure frequency.

Suicidal Behavior and Ideation

Antiepileptic drugs (AEDs) including Felbatol®, increase the risk of suicidal thoughts or behavior in patients taking these drugs for any indication. Patients treated with any AED for any indication should be monitored for the emergence or worsening of depression, suicidal thoughts or behavior, and/or any unusual changes in mood or behavior.

Pooled analyses of 199 placebo-controlled clinical trials (mono- and adjunctive therapy) of 11 different AEDs showed that patients randomized to one of the AEDs had approximately twice the risk (adjusted Relative Risk 1.8, 95% CI:1.2, 2.7) of suicidal thinking or behavior compared to patients randomized to placebo. In these trials, which had a median treatment duration of 12 weeks, the estimated incidence rate of suicidal behavior or ideation among 27,863 AED-treated patients was 0.43%, compared to 0.24% among 16,029 placebo-treated patients, representing an increase of approximately one case of suicidal thinking or behavior for every 530 patients treated. There were four suicides in drug-treated patients in the trials and none in placebo-treated patients, but the number is too small to allow any conclusion about drug effect on suicide.

The increased risk of suicidal thoughts or behavior with AEDs was observed as early as one week after starting drug treatment with AEDs and persisted for the duration of treatment assessed. Because most trials included in the analysis did not extend beyond 24 weeks, the risk of suicidal thoughts or behavior beyond 24 weeks could not be assessed.

The risk of suicidal thoughts or behavior was generally consistent among drugs in the data analyzed. The finding of increased risk with AEDs of varying mechanisms of action and across a range of indications suggests that the risk applies to all AEDs used for any indication. The risk did not vary substantially by age (5-100 years) in the clinical trials analyzed.

Table 1 shows absolute and relative risk by indication for all evaluated AEDs.

Table 1 Risk by Indication for Antiepileptic Drugs in the Pooled Analysis
Indication | Placebo; Patients with Events Per; 1000 Patients | Drug Patients; with Events; Per 1000; Patients | Relative Risk:; Incidence of; Events in Drug; Patients/Incidence; in Placebo; Patients | Risk Difference:; Additional Drug; Patients with; Events Per; 1000 Patients
Epilepsy | 1.0 | 3.4 | 3.5 | 2.4
Psychiatric | 5.7 | 8.5 | 1.5 | 2.9
Other | 1.0 | 1.8 | 1.9 | 0.9
Total | 2.4 | 4.3 | 1.8 | 1.9

The relative risk for suicidal thoughts or behavior was higher in clinical trials for epilepsy than in clinical trials for psychiatric or other conditions, but the absolute risk differences were similar for the epilepsy and psychiatric indications.

Anyone considering prescribing Felbatol® or any other AED must balance the risk of suicidal thoughts or behavior with the risk of untreated illness. Epilepsy and many other illnesses for which AEDs are prescribed are themselves associated with morbidity and mortality and an increased risk of suicidal thoughts and behavior. Should suicidal thoughts and behavior emerge during treatment, the prescriber needs to consider whether the emergence of these symptoms in any given patient may be related to the illness being treated.

Patients, their caregivers, and families should be informed that AEDs increase the risk of suicidal thoughts and behavior and should be advised of the need to be alert for the emergence or worsening of the signs and symptoms of depression, any unusual changes in mood or behavior, or the emergence of suicidal thoughts, behavior, or thoughts about self-harm. Behaviors of concern should be reported immediately to healthcare providers.

PRECAUTIONS

Dosage Adjustment in the Renally Impaired

A study in otherwise healthy individuals with renal dysfunction indicated that prolonged half-life and reduced clearance of felbamate are associated with diminishing renal function. Felbamate should be used with caution in patients with renal dysfunction (see DOSAGE AND ADMINISTRATION).

Information for Patients

Patients should be informed that the use of Felbatol® is associated with aplastic anemia and hepatic failure, potentially fatal conditions acutely or over a long term.

The physician should obtain written acknowledgment prior to initiation of Felbatol® therapy (see PATIENT/PHYSICIAN ACKNOWLEDGMENT FORM section).

Patients should be instructed to read the Medication Guide supplied as required by law when Felbatol® is dispensed. The complete text of the Medication Guide is reprinted at the end of this document.

Aplastic anemia in the general population is relatively rare. The absolute risk for the individual patient is not known with any degree of reliability, but patients on Felbatol® may be at more than a 100 fold greater risk for developing the syndrome than the general population.

The long term outlook for patients with aplastic anemia is variable. Although many patients are apparently cured, others require repeated transfusions and other treatments for relapses, and some, although surviving for years, ultimately develop serious complications that sometimes prove fatal (e.g., leukemia).

At present there is no way to predict who is likely to get aplastic anemia, nor is there a documented effective means to monitor the patient so as to avoid and/or reduce the risk. Patients with a history of any blood dyscrasia should not receive Felbatol®.

Patients should be advised to be alert for signs of infection, bleeding, easy bruising, or signs of anemia (fatigue, weakness, lassitude, etc.) and should be advised to report to the physician immediately if any such signs or symptoms appear.

Hepatic failure in the general population is relatively rare. The absolute risk for an individual patient is not known with any degree of reliability but patients on Felbatol® are at a greater risk for developing hepatic failure than the general population.

At present, there is no way to predict who is likely to develop hepatic failure, however, patients with a history of hepatic dysfunction should not be started on Felbatol®.

Patients should be advised to follow their physician’s directives for liver function testing both before starting Felbatol® and at frequent intervals while taking Felbatol®.

Patients should be advised to be alert for signs of liver dysfunction (jaundice, anorexia, gastrointestinal complaints, malaise, etc.) and to report them to their doctor immediately if they should occur.

Laboratory Tests

Full hematologic evaluations should be performed before Felbatol® therapy, frequently during therapy, and for a significant period of time after discontinuation of Felbatol® therapy. While it might appear prudent to perform frequent CBCs in patients continuing on Felbatol®, there is no evidence that such monitoring will allow early detection of marrow suppression before aplastic anemia occurs. (see Boxed Warnings). Complete pretreatment blood counts, including platelets and reticulocytes should be obtained as a baseline. If any hematologic abnormalities are detected during the course of treatment, immediate consultation with a hematologist is advised. Felbatol® should be discontinued if any evidence of bone marrow depression occurs.

See Box Warnings for recommended monitoring of serum transaminases. If significant, confirmed liver abnormalities are detected during the course of Felbatol® treatment, Felbatol® should be discontinued immediately with continued liver function monitoring until values return to normal. (see PATIENT/PHYSICIAN ACKNOWLEDGMENT FORM).

Suicidal Thinking and Behavior

Patients, their caregivers, and families should be counseled that AEDs, including Felbatol®, may increase the risk of suicidal thoughts and behavior and should be advised of the need to be alert for the emergence or worsening of symptoms of depression, any unusual changes in mood or behavior, or the emergence of suicidal thoughts, behavior, or thoughts about self-harm. Behaviors of concern should be reported immediately to healthcare providers.

Pregnancy

Patients should be encouraged to enroll in the North American Antiepileptic Drug (NAAED) Pregnancy Registry if they become pregnant. This registry is collecting information about the safety of antiepileptic drugs during pregnancy. To enroll, patients can call the toll free number 1-888-233-2334 (see Pregnancy section).

Drug Interactions

The drug interaction data described in this section were obtained from controlled clinical trials and studies involving otherwise healthy adults with epilepsy.

Use in Conjunction with Other Antiepileptic Drugs (see DOSAGE AND ADMINISTRATION)

The addition of Felbatol® to antiepileptic drugs (AEDs) affects the steady-state plasmaconcentrations of AEDs. The net effect of these interactions is summarized in Table 2:

Table 2 Steady-State Plasma Concentrations of Felbatol When Coadministered With Other AEDs
AED; Coadministered | AED; Concentration | Felbatol®; Concentration
Phenytoin | ↑ | ↓
Valproate | ↑ | ↔ [No significant effect.]
Carbamazepine (CBZ); [Not administered, but an active metabolite of carbamazepine.] CBZ epoxide | ↓; ↑ | ↓
Phenobarbital | ↑ | ↓

Specific Effects of Felbatol® on Other Antiepileptic Drugs

Phenytoin

Felbatol® causes an increase in steady-state phenytoin plasma concentrations. In 10 otherwise healthy subjects with epilepsy ingesting phenytoin, the steady-state trough (Cmin) phenytoin plasma concentration was 17±5 micrograms/mL. The steady-state Cmin increased to 21±5 micrograms/mL when 1200 mg/day of felbamate was coadministered. Increasing the felbamate dose to 1800 mg/day in six of these subjects increased the steady-state phenytoin Cmin to 25±7 micrograms/mL. In order to maintain phenytoin levels, limit adverse experiences, and achieve the felbamate dose of 3600 mg/day, a phenytoin dose reduction of approximately 40% was necessary for eight of these 10 subjects.

In a controlled clinical trial, a 20% reduction of the phenytoin dose at the initiation of Felbatol® therapy resulted in phenytoin levels comparable to those prior to Felbatol® administration.

Carbamazepine

Felbatol® causes a decrease in the steady-state carbamazepine plasma concentrations and an increase in the steady-state carbamazepine epoxide plasma concentration. In nine otherwise healthy subjects with epilepsy ingesting carbamazepine, the steady-state trough (Cmin) carbamazepine concentration was 8±2 micrograms/mL. The carbamazepine steady-state Cmin decreased 31% to 5±1 micrograms/mL when felbamate (3000 mg/day, divided into three doses) was coadministered. Carbamazepine epoxide steady-state Cmin concentrations increased 57% from 1.0±0.3 to 1.6±0.4 micrograms/mL with the addition of felbamate.

In clinical trials, similar changes in carbamazepine and carbamazepine epoxide were seen.

Valproate

Felbatol® causes an increase in steady-state valproate concentrations. In four subjects with epilepsy ingesting valproate, the steady-state trough (Cmin) valproate plasma concentration was 63±16 micrograms/mL. The steady-state Cmin increased to 78±14 micrograms/mL when 1200 mg/day of felbamate was coadministered. Increasing the felbamate dose to 2400 mg/day increased the steady-state valproate Cmin to 96±25 micrograms/mL. Corresponding values for free valproate Cmin concentrations were 7±3, 9±4, and 11±6 micrograms/mL for 0, 1200, and 2400 mg/day Felbatol®, respectively. The ratios of the AUCs of unbound valproate to the AUCs of the total valproate were 11.1%, 13.0%, and 11.5%, with coadministration of 0, 1200, and 2400 mg/day of Felbatol®, respectively. This indicates that the protein binding of valproate did not change appreciably with increasing doses of Felbatol®.

Phenobarbital

Coadministration of felbamate with phenobarbital causes an increase in phenobarbital plasma concentrations. In 12 otherwise healthy male volunteers ingesting phenobarbital, the steady-state trough (Cmin) phenobarbital concentration was 14.2 micrograms/mL. The steady-state Cmin concentration increased to 17.8 micrograms/mL when 2400 mg/day of felbamate was coadministered for one week.

Effects of Other Antiepileptic Drugs on Felbatol®

Phenytoin

Phenytoin causes an approximate doubling of the clearance of Felbatol® (felbamate) at steady-state and, therefore, the addition of phenytoin causes an approximate 45% decrease in the steady-state trough concentrations of Felbatol® as compared to the same dose of Felbatol® given as monotherapy.

Carbamazepine

Carbamazepine causes an approximate 50% increase in the clearance of Felbatol® at steady-state and, therefore, the addition of carbamazepine results in an approximate 40% decrease in the steady-state trough concentrations of Felbatol® as compared to the same dose of Felbatol® given as monotherapy.

Valproate

Available data suggest that there is no significant effect of valproate on the clearance of Felbatol® at steady-state. Therefore, the addition of valproate is not expected to cause a clinically important effect on Felbatol® (felbamate) plasma concentrations.

Phenobarbital

It appears that phenobarbital may reduce plasma felbamate concentrations. Steady-state plasma felbamate concentrations were found to be 29% lower than the mean concentrations of a group of newly diagnosed subjects with epilepsy also receiving 2400 mg of felbamate a day.

Effects of Antacids on Felbatol®

The rate and extent of absorption of a 2400 mg dose of Felbatol® as monotherapy given as tablets was not affected when coadministered with antacids.

Effects of Erythromycin on Felbatol®

The coadministration of erythromycin (1000 mg/day) for 10 days did not alter the pharmacokinetic parameters of Cmax, Cmin, AUC, Cl/kg or Tmax at felbamate daily doses of 3000 or 3600 mg/day in 10 otherwise healthy subjects with epilepsy.

Effects of Felbatol® on Low-Dose Combination Oral Contraceptives

A group of 24 nonsmoking, healthy white female volunteers established on an oral contraceptive regimen containing 30 µg ethinyl estradiol and 75 µg gestodene for at least 3 months received 2400 mg/day of felbamate from midcycle (day 15) to midcycle (day 14) of two consecutive oral contraceptive cycles. Felbamate treatment resulted in a 42% decrease in the gestodene AUC 0-24, but no clinically relevant effect was observed on the pharmacokinetic parameters of ethinyl estradiol. No volunteer showed hormonal evidence of ovulation, but one volunteer reported intermenstrual bleeding during felbamate treatment.

Drug/Laboratory Test Interactions

There are no known interactions of Felbatol® with commonly used laboratory tests.

Carcinogenesis, Mutagenesis, Impairment of Fertility

Carcinogenicity studies were conducted in mice and rats. Mice received felbamate as a feed admixture for 92 weeks at doses of 300, 600, and 1200 mg/kg and rats were also dosed by feed admixture for 104 weeks at doses of 30, 100, and 300 (males) or 10, 30, and 100 (females) mg/kg. The maximum doses in these studies produced steady-state plasma concentrations that were equal to or less than the steady-state plasma concentrations in epileptic patients receiving 3600 mg/day. There was a statistically significant increase in hepatic cell adenomas in high-dose male and female mice and in high-dose female rats. Hepatic hypertrophy was significantly increased in a dose-related manner in mice, primarily males, but also in females. Hepatic hypertrophy was not found in female rats. The relationship between the occurrence of benign hepatocellular adenomas and the finding of liver hypertrophy resulting from liver enzyme induction has not been examined. There was a statistically significant increase in benign interstitial cell tumors of the testes in high-dose male rats receiving felbamate. The relevance of these findings to humans is unknown.

As a result of the synthesis process, felbamate could contain small amounts of two known animal carcinogens, the genotoxic compound ethyl carbamate (urethane) and the nongenotoxic compound methyl carbamate. It is theoretically possible that a 50 kg patient receiving 3600 mg of felbamate could be exposed to up to 0.72 micrograms of urethane and 1800 micrograms of methyl carbamate. These daily doses are approximately 1/35,000 (urethane) and 1/5,500 (methyl carbamate) on a mg/kg basis, and 1/10,000 (urethane) and 1/1,600 (methyl carbamate) on a mg/m^2 basis, of the dose levels shown to be carcinogenic in rodents. Any presence of these two compounds in felbamate used in the lifetime carcinogenicity studies was inadequate to cause tumors.

Microbial and mammalian cell assays revealed no evidence of mutagenesis in the Ames Salmonella/microsome plate test, CHO/HGPRT mammalian cell forward gene mutation assay, sister chromatid exchange assay in CHO cells, and bone marrow cytogenetics assay.

Reproduction and fertility studies in rats showed no effects on male or female fertility at oral doses of up to 13.9 times the human total daily dose of 3600 mg on a mg/kg basis, or up to 3 times the human total daily dose on a mg/m^2 basis.

Pregnancy

The incidence of malformations was not increased compared to control in offspring of rats or rabbits given doses up to 13.9 times (rat) and 4.2 times (rabbit) the human daily dose on a mg/kg basis, or 3 times (rat) and less than 2 times (rabbit) the human daily dose on a mg/m^2 basis. However, in rats, there was a decrease in pup weight and an increase in pup deaths during lactation. The cause for these deaths is not known. The no effect dose for rat pup mortality was 6.9 times the human dose on a mg/kg basis or 1.5 times the human dose on a mg/m^2 basis.

Placental transfer of felbamate occurs in rat pups. There are, however, no studies in pregnant women. Because animal reproduction studies are not always predictive of human response, this drug should be used during pregnancy only if clearly needed.

To provide information regarding the effects of in utero exposure to Felbatol®, physicians are advised to recommend that pregnant patients taking Felbatol enroll in the NAAED Pregnancy Registry. This can be done by calling the toll free number 1-888-233-2334, and must be done by patients themselves. Information on the registry can also be found at the website http://www.aedpregnancyregistry.org/.

Labor and Delivery

The effect of felbamate on labor and delivery in humans is unknown.

Nursing Mothers

Felbamate has been detected in human milk. The effect on the nursing infant is unknown (see Pregnancy section).

Pediatric Use

The safety and effectiveness of Felbatol® in children other than those with Lennox-Gastaut syndrome has not been established.

Geriatric Use

No systematic studies in geriatric patients have been conducted. Clinical studies of Felbatol® did not include sufficient numbers of patients aged 65 and over to determine whether they respond differently from younger patients. Other reported clinical experience has not identified differences in responses between the elderly and younger patients. In general, dosage selection for an elderly patient should be cautious, usually starting at the low end of the dosing range, reflecting the greater frequency of decreased hepatic, renal, or cardiac function, and of concomitant disease or other drug therapy.

ADVERSE REACTIONS

To report SUSPECTED ADVERSE REACTIONS, contact Viatris at 1-877-446-3679 (1-877-4-INFO-RX) or FDA at 1-800-FDA-1088 or www.fda.gov/medwatch.

The most common adverse reactions seen in association with Felbatol® (felbamate) in adults during monotherapy are anorexia, vomiting, insomnia, nausea, and headache. The most common adverse reactions seen in association with Felbatol® in adults during adjunctive therapy are anorexia, vomiting, insomnia, nausea, dizziness, somnolence, and headache.

The most common adverse reactions seen in association with Felbatol® in children during adjunctive therapy are anorexia, vomiting, insomnia, headache, and somnolence.

The dropout rate because of adverse experiences or intercurrent illnesses among adult felbamate patients was 12 percent (120/977). The dropout rate because of adverse experiences or intercurrent illnesses among pediatric felbamate patients was six percent (22/357). In adults, the body systems associated with causing these withdrawals in order of frequency were: digestive (4.3%), psychological (2.2%), whole body (1.7%), neurological (1.5%), and dermatological (1.5%). In children, the body systems associated with causing these withdrawals in order of frequency were: digestive (1.7%), neurological (1.4%), dermatological (1.4%), psychological (1.1%), and whole body (1.0%). In adults, specific events with an incidence of 1% or greater associated with causing these withdrawals, in order of frequency were: anorexia (1.6%), nausea (1.4%), rash (1.2%), and weight decrease (1.1%). In children, specific events with an incidence of 1% or greater associated with causing these withdrawals, in order of frequency was rash (1.1%).

Incidence in Clinical Trials

The prescriber should be aware that the figures cited in the following table cannot be used to predict the incidence of side effects in the course of usual medical practice where patient characteristics and other factors differ from those which prevailed in the clinical trials. Similarly, the cited frequencies cannot be compared with figures obtained from other clinical investigations involving different investigators, treatments, and uses including the use of Felbatol® (felbamate) as adjunctive therapy where the incidence of adverse events may be higher due to drug interactions. The cited figures, however, do provide the prescribing physician with some basis for estimating the relative contribution of drug and nondrug factors to the side effect incidence rate in the population studied.

Adults

Incidence in Controlled Clinical Trials – Monotherapy Studies in Adults

The table that follows enumerates adverse events that occurred at an incidence of 2% or more among 58 adult patients who received Felbatol® monotherapy at dosages of 3600 mg/day in double-blind controlled trials. Table 3 presents reported adverse events that were classified using standard WHO-based dictionary terminology.

Table 3 Adults Treatment-Emergent Adverse Event Incidence in Controlled Monotherapy Trials
 | Felbatol® [3600 mg/day] (N=58) | Low Dose; Valproate [15 mg/kg/day] (N=50)
Body System/Event | % | %
Body as a Whole; Fatigue; Weight Decrease; Face Edema | 6.9; 3.4; 3.4 | 4.0; 0; 0
Central Nervous System; Insomnia; Headache; Anxiety | 8.6; 6.9; 5.2 | 4.0; 18.0; 2.0
Dermatological; Acne; Rash | 3.4; 3.4 | 0; 0
Digestive; Dyspepsia; Vomiting; Constipation; Diarrhea; SGPT Increased | 8.6; 8.6; 6.9; 5.2; 5.2 | 2.0; 2.0; 2.0; 0; 2.0
Metabolic/Nutritional; Hypophosphatemia | 3.4 | 0
Respiratory; Upper Respiratory Tract Infection; Rhinitis | 8.6; 6.9 | 4.0; 0
Special Senses; Diplopia; Otitis Media | 3.4; 3.4 | 4.0; 0
Urogenital; Intramenstrual Bleeding; Urinary Tract Infection | 3.4; 3.4 | 0; 2.0

Incidence in Controlled Add-On Clinical Studies in Adults

Table 4 enumerates adverse events that occurred at an incidence of 2% or more among 114 adult patients who received Felbatol® adjunctive therapy in add-on controlled trials at dosages up to 3600 mg/day. Reported adverse events were classified using standard WHO-based dictionary terminology.

Many adverse experiences that occurred during adjunctive therapy may be a result of drug interactions. Adverse experiences during adjunctive therapy typically resolved with conversion to monotherapy, or with adjustment of the dosage of other antiepileptic drugs.

Table 4 Adults Treatment-Emergent Adverse Event Incidence in Controlled Add-On Trials
 | Felbatol® (N=114) | Placebo (N=43)
Body System/Event | % | %
Body as a Whole; Fatigue; Fever; Chest Pain | 16.8; 2.6; 2.6 | 7.0; 4.7; 0
Central Nervous System; Headache; Somnolence; Dizziness; Insomnia; Nervousness; Tremor; Anxiety; Gait Abnormal; Depression; Paraesthesia; Ataxia; Mouth Dry; Stupor | 36.8; 19.3; 18.4; 17.5; 7.0; 6.1; 5.3; 5.3; 5.3; 3.5; 3.5; 2.6; 2.6 | 9.3; 7.0; 14.0; 7.0; 2.3; 2.3; 4.7; 0; 0; 2.3; 0; 0; 0
Dermatological; Rash | 3.5 | 4.7
Digestive; Nausea; Anorexia; Vomiting; Dyspepsia; Constipation; Diarrhea; Abdominal Pain; SGPT Increased | 34.2; 19.3; 16.7; 12.3; 11.4; 5.3; 5.3; 3.5 | 2.3; 2.3; 4.7; 7.0; 2.3; 2.3; 0; 0
Musculoskeletal; Myalgia | 2.6 | 0
Respiratory; Upper Respiratory Tract Infection; Sinusitis; Pharyngitis | 5.3; 3.5; 2.6 | 7.0; 0; 0
Special Senses; Diplopia; Taste Perversion; Vision Abnormal | 6.1; 6.1; 5.3 | 0; 0; 2.3

Children

Incidence in a Controlled Add-On Trial in Children with Lennox-Gastaut Syndrome

Table 5 enumerates adverse events that occurred more than once among 31 pediatric patients who received Felbatol® up to 45 mg/kg/day or a maximum of 3600 mg/day. Reported adverse events were classified using standard WHO-based dictionary terminology.

Table 5 Children Treatment-Emergent Adverse Event Incidence in Controlled Add-On Lennox-Gaustat Trials
 | Felbatol® (N=31) | Placebo (N=27)
Body System/Event | % | %
Body as a Whole; Fever; Fatigue; Weight Decrease; Pain | 22.6; 9.7; 6.5; 6.5 | 11.1; 3.7; 0; 0
Central Nervous System; Somnolence; Insomnia; Nervousness; Gait Abnormal; Headache; Thinking Abnormal; Ataxia; Urinary Incontinence; Emotional Lability; Miosis | 48.4; 16.1; 16.1; 9.7; 6.5; 6.5; 6.5; 6.5; 6.5; 6.5 | 11.1; 14.8; 18.5; 0; 18.5; 3.7; 3.7; 7.4; 0; 0
Dermatological; Rash | 9.7 | 7.4
Digestive; Anorexia; Vomiting; Constipation; Hiccup; Nausea; Dyspepsia | 54.8; 38.7; 12.9; 9.7; 6.5; 6.5 | 14.8; 14.8; 0; 3.7; 0; 3.7
Hematologic; Purpura; Leukopenia | 12.9; 6.5 | 7.4; 0
Respiratory; Upper Respiratory Tract Infection; Pharyngitis; Coughing | 45.2; 9.7; 6.5 | 25.9; 3.7; 0
Special Senses; Otitis Media | 9.7 | 0

Other Events Observed in Association with the Administration of Felbatol® (felbamate)

In the paragraphs that follow, the adverse clinical events, other than those in the preceding tables, that occurred in a total of 977 adults and 357 children exposed to Felbatol® (felbamate) and that are reasonably associated with its use are presented. They are listed in order of decreasing frequency. Because the reports cite events observed in open-label and uncontrolled studies, the role of Felbatol® in their causation cannot be reliably determined.

Events are classified within body system categories and enumerated in order of decreasing frequency using the following definitions: frequent adverse events are defined as those occurring on one or more occasions in at least 1/100 patients; infrequent adverse events are those occurring in 1/100–1/1000 patients; and rare events are those occurring in fewer than 1/1000 patients.

Event frequencies are calculated as the number of patients reporting an event divided by the total number of patients (N=1334) exposed to Felbatol®.

Body as a Whole: Frequent: Weight increase, asthenia, malaise, influenza-like symptoms; Rare: anaphylactoid reaction, chest pain substernal.

Cardiovascular: Frequent: Palpitation, tachycardia; Rare: supraventricular tachycardia.

Central Nervous System: Frequent: Agitation, psychological disturbance, aggressive reaction; Infrequent: hallucination, euphoria, suicide attempt, migraine.

Digestive: Frequent: SGOT increased; Infrequent: esophagitis, appetite increased; Rare: GGT elevated.

Hematologic: Infrequent: Lymphadenopathy, leukopenia, leukocytosis, thrombocytopenia, granulocytopenia; Rare: antinuclear factor test positive, qualitative platelet disorder, agranulocytosis.

Metabolic/Nutritional: Infrequent: Hypokalemia, hyponatremia, LDH increased, alkaline phosphatase increased, hypophosphatemia; Rare: creatinine phosphokinase increased.

Musculoskeletal: Infrequent: Dystonia.

Dermatological: Frequent: Pruritus; Infrequent: urticaria, bullous eruption; Rare: buccal mucous membrane swelling, Stevens-Johnson Syndrome.

Special Senses: Rare: Photosensitivity allergic reaction.

Postmarketing Adverse Event Reports

Voluntary reports of adverse events in patients taking Felbatol® (usually in conjunction with other drugs) have been received since market introduction and may have no causal relationship with the drug(s). These include the following by body system:

Body as a Whole: neoplasm, sepsis, L.E. syndrome, SIDS, sudden death, edema, hypothermia, rigors, hyperpyrexia.

Cardiovascular: atrial fibrillation, atrial arrhythmia, cardiac arrest, torsade de pointes, cardiac failure, hypotension, hypertension, flushing, thrombophlebitis, ischemic necrosis, gangrene, peripheral ischemia, bradycardia, Henoch-Schönlein purpura (vasculitis).

Central & Peripheral Nervous System: delusion, paralysis, mononeuritis, cerebrovascular disorder, cerebral edema, coma, manic reaction, encephalopathy, paranoid reaction, nystagmus, choreoathetosis, extrapyramidal disorder, confusion, psychosis, status epilepticus, dyskinesia, dysarthria, respiratory depression, apathy, concentration impaired.

Dermatological: abnormal body odor, sweating, lichen planus, livedo reticularis, alopecia, toxic epidermal necrolysis.

Digestive: (Refer to WARNINGS) hepatitis, hepatic failure, G.I. hemorrhage, hyperammonemia, pancreatitis, hematemesis, gastritis, rectal hemorrhage, flatulence, gingival bleeding, acquired megacolon, ileus, intestinal obstruction, enteritis, ulcerative stomatitis, glossitis, dysphagia, jaundice, gastric ulcer, gastric dilation, gastroesophageal reflux.

Fetal Disorders: fetal death, microcephaly, genital malformation, anencephaly, encephalocele.

Hematologic: (Refer to WARNINGS) increased and decreased prothrombin time, anemia, hypochromic anemia, aplastic anemia, pancytopenia, hemolytic uremic syndrome, increased mean corpuscular volume (mcv) with and without anemia, coagulation disorder, embolism-limb, disseminated intravascular coagulation, eosinophilia, hemolytic anemia, leukemia, including myelogenous leukemia, and lymphoma, including T-cell and B-cell lymphoproliferative disorders.

Metabolic/Nutritional: hypernatremia, hypoglycemia, SIADH, hypomagnesemia, dehydration, hyperglycemia, hypocalcemia.

Musculoskeletal: arthralgia, muscle weakness, involuntary muscle contraction, rhabdomyolysis.

Respiratory: dyspnea, pneumonia, pneumonitis, hypoxia, epistaxis, pleural effusion, respiratory insufficiency, pulmonary hemorrhage, asthma.

Special Senses: hemianopsia, decreased hearing, conjunctivitis.

Urogenital: menstrual disorder, acute renal failure, hepatorenal syndrome, hematuria, urinary retention, nephrosis, vaginal hemorrhage, abnormal renal function, dysuria, placental disorder.

DRUG ABUSE AND DEPENDENCE

Abuse

Abuse potential was not evaluated in human studies.

Dependence

Rats administered felbamate orally at doses 8.3 times the recommended human dose 6 days each week for 5 consecutive weeks demonstrated no signs of physical dependence as measured by weight loss following drug withdrawal on day 7 of each week.

OVERDOSAGE

Four subjects inadvertently received Felbatol® (felbamate) as adjunctive therapy in dosages ranging from 5400 to 7200 mg/day for durations between 6 and 51 days. One subject who received 5400 mg/day as monotherapy for 1 week reported no adverse experiences. Another subject attempted suicide by ingesting 12,000 mg of Felbatol® in a 12-hour period. The only adverse experiences reported were mild gastric distress and a resting heart rate of 100 bpm. No serious adverse reactions have been reported.

General supportive measures should be employed if overdosage occurs. It is not known if felbamate is dialyzable.

DOSAGE AND ADMINISTRATION

Felbatol® (felbamate) has been studied as monotherapy and adjunctive therapy in adults and as adjunctive therapy in children with seizures associated with Lennox-Gastaut syndrome. As Felbatol® is added to or substituted for existing AEDs, it is strongly recommended to reduce the dosage of those AEDs in the range of 20–33% to minimize side effects (see Drug Interactions subsection).

Dosage Adjustment in the Renally Impaired

Felbamate should be used with caution in patients with renal dysfunction. In the renally impaired, starting and maintenance doses should be reduced by one-half (see CLINICAL PHARMACOLOGY/Pharmacokinetics and PRECAUTIONS). Adjunctive therapy with medications which affect felbamate plasma concentrations, especially AEDs, may warrant further reductions in felbamate daily doses in patients with renal dysfunction.

Adults (14 years of age and over)

The majority of patients received 3600 mg/day in clinical trials evaluating its use as both monotherapy and adjunctive therapy.

Monotherapy: (Initial therapy) Felbatol® (felbamate) has not been systematically evaluated as initial monotherapy. Initiate Felbatol® (felbamate) at 1200 mg/day in divided doses three or four times daily. The prescriber is advised to titrate previously untreated patients under close clinical supervision, increasing the dosage in 600-mg increments every 2 weeks to 2400 mg/day based on clinical response and thereafter to 3600 mg/day if clinically indicated.

Conversion to Monotherapy: Initiate Felbatol® at 1200 mg/day in divided doses three or four times daily. Reduce the dosage of concomitant AEDs by one-third at initiation of Felbatol® therapy. At week 2, increase the Felbatol® dosage to 2400 mg/day while reducing the dosage of other AEDs up to an additional one-third of their original dosage. At week 3, increase the Felbatol® dosage up to 3600 mg/day and continue to reduce the dosage of other AEDs as clinically indicated.

Adjunctive Therapy: Felbatol® should be added at 1200 mg/day in divided doses three or four times daily while reducing present AEDs by 20% in order to control plasma concentrations of concurrent phenytoin, valproic acid, phenobarbital, and carbamazepine and its metabolites. Further reductions of the concomitant AEDs dosage may be necessary to minimize side effects due to drug interactions. Increase the dosage of Felbatol® by 1200 mg/day increments at weekly intervals to 3600 mg/day. Most side effects seen during Felbatol® adjunctive therapy resolve as the dosage of concomitant AEDs is decreased.

Table 6 Dosage Table (adults)
Dosage reduction of concomitant AEDs | WEEK 1; REDUCE original dose by; 20–33% [See Adjunctive and Conversion to Monotherapy sections.] | WEEK 2; REDUCE original dose by up to an additional 1/3 | WEEK 3; REDUCE as clinically; indicated
Felbatol®; Dosage | 1200 mg/day; Initial dose | 2400 mg/day; Therapeutic; dosage range | 3600 mg/day; Therapeutic; dosage range

While the above Felbatol® conversion guidelines may result in a Felbatol® 3600 mg/day dose within 3 weeks, in some patients titration to a 3600 mg/day Felbatol® dose has been achieved in as little as 3 days with appropriate adjustment of other AEDs.

Children with Lennox-Gastaut Syndrome (Ages 2–14 years)

Adjunctive Therapy: Felbatol® should be added at 15 mg/kg/day in divided doses three or four times daily while reducing present AEDs by 20% in order to control plasma levels of concurrent phenytoin, valproic acid, phenobarbital, and carbamazepine and its metabolites. Further reductions of the concomitant AEDs dosage may be necessary to minimize side effects due to drug interactions. Increase the dosage of Felbatol® by 15 mg/kg/day increments at weekly intervals to 45 mg/kg/day. Most side effects seen during Felbatol® adjunctive therapy resolve as the dosage of concomitant AEDs is decreased.

HOW SUPPLIED

Felbatol® (felbamate) Tablets, 400 mg, are yellow, scored, capsule-shaped tablets, debossed 0430 on one side and FELBATOL 400 on the other; available in bottles of 100 (NDC 0037 0430-01). Felbatol® (felbamate) Tablets, 600 mg, are peach-colored, scored, capsule-shaped tablets, debossed 0431 on one side and FELBATOL 600 on the other; available in bottles of 100 (NDC 0037-0431-01). Felbatol® (felbamate) Oral Suspension, 600 mg/5 mL, is peach-colored; available in 8 oz bottles (NDC 0037-0442-67) and 32 oz bottles (NDC 0037-0442-17).

Shake suspension well before using. Store at controlled room temperature 20°–25°C (68°–77°F). Dispense in tight container.

PATIENT/PHYSICIAN ACKNOWLEDGMENT FORM

FELBATOL® (felbamate) SHOULD NOT BE USED BY PATIENTS UNTIL THERE HAS BEEN A COMPLETE DISCUSSION OF THE RISKS.

All patients treated with Felbatol should acknowledge that they understand the risks and other information about Felbatol discussed below, and physicians should acknowledge this discussion.

IMPORTANT INFORMATION AND WARNING:

Felbatol®, taken by itself or with other prescription and/or non-prescription drugs, can result in a severe, potentially fatal blood abnormality (“aplastic anemia”) and/or severe, potentially fatal liver damage.

PATIENT ACKNOWLEDGMENT:

Do not sign this form if there is anything you do not understand about the information you have received. Ask your doctor about anything you do not understand before you initial any of the items below or sign this form.

My [My son, daughter, ward, __________________________________________________’s]

treatment with Felbatol® has been personally explained to me by
Dr. ______________________________.

The following points of information, among others, have been specifically discussed and made clear and I have had the opportunity to ask any questions concerning this information:

1. I, __________________________________________________________(Patient’s Name), understand that Felbatol® is used to treat certain types of seizures and my physician has told me that I have this type(s) of seizures;

INITIALS: __________

2. I understand that Felbatol® is being used because my seizures have not been satisfactorily treated with other antiepileptic drugs;

INITIALS: __________

3. I understand that there is a serious risk that I could develop aplastic anemia and/or liver failure, both of which are potentially fatal, by using Felbatol®;

INITIALS: __________

4. I understand that there are no laboratory tests which will predict if I am at an increased risk for one of the potentially fatal conditions;

INITIALS: __________

5. I understand that I should have the recommended blood work before my treatment with Felbatol® is begun (baseline) and periodically thereafter as clinical judgement warrants. I understand that although this blood work may help detect if I develop one of these conditions, it may do so only after significant, irreversible and potentially fatal damage has already occurred;

INITIALS: __________

6. If I am currently taking other antiepileptic drugs, I understand that the manufacturer of Felbatol® recommends that the dosage of these other drugs be decreased by a certain amount when Felbatol® is started; if my physician determines that this should not be done in my case, he/she has explained the reason(s) for this decision;

INITIALS: __________

7. I understand that I must immediately report any unusual symptoms to Dr._______________and be especially aware of any rashes, easy bruising, bleeding, sore throats, fever, and/or dark urine;

INITIALS: __________

8. I understand that antiepileptic drugs such as Felbatol® may increase the risk of suicidal thoughts and behavior. I understand that I must immediately report any unusual changes in mood or behavior, symptoms of depression or thoughts about self-harm to Dr._________________.

INITIALS: __________

____________________________________________________________________________

Patient, Parent, or Guardian

____________________________________________________________________________

Address

____________________________________________________________________________

Telephone

PHYSICIAN STATEMENT:

I have fully explained to the patient, ______________________________________________, the nature and purpose of the treatment with Felbatol® (felbamate) and the potential risks associated with that treatment. I have asked the patient if he/she has any questions regarding this treatment or the risks and have answered those questions to the best of my ability. I also acknowledge that I have read and understand the prescribing information.

____________________________________________________________________________

Physician Date

Revised 7/11

NOTE TO PHYSICIAN: It is strongly recommended that you retain a signed copy of the Patient/Physician Acknowledgment Form with the patient’s medical records.

SUPPLY OF PATIENT/PHYSICIAN ACKNOWLEDGMENT FORMS:

A supply of “Patient/Physician Acknowledgment” Forms as printed above is available, free of charge by calling 1-877-446-3679 (1-877-4-INFO-RX). Permission to use the above Patient/Physician Acknowledgment Form by photocopy reproduction is also hereby granted by Viatris Specialty LLC.

For more information, call Viatris at 1-877-446-3679 (1-877-4-INFO-RX).

FELBATOL is a registered trademark of Meda Pharmaceuticals Inc., a Viatris Company.

© 2025 Viatris Inc.

Distributed by:
Viatris Specialty LLC
Morgantown, WV 26505 U.S.A.

201110-01
Revised: 8/2025

VS:SOV:FELT:R1m/VS:SOV:MG:FELT:R1m

Medication Guide

FELBATOL (Fel-ba-taal) (felbamate)

Tablets and Oral Suspension

Read this Medication Guide before you start taking FELBATOL and each time you get a refill. There may be new information. This information does not take the place of talking to your healthcare provider about your medical condition or treatment.

What is the most important information I should know about FELBATOL?

Do not stop taking FELBATOL without first talking to your healthcare provider.

Stopping FELBATOL suddenly can cause serious problems.

FELBATOL can cause serious side effects, including:

1. FELBATOL may cause serious blood problems that may be life-threatening.

Call your healthcare provider right away if you have any of the following symptoms:

- Fever, sore throat or other infections that come and go or do not go away
- Frequent infections or an infection that does not go away
- Easy bruising
- Red or purple spots on your body
- Bleeding gums or nose bleeds
- Severe fatigue or weakness

2. Liver problems that may be life-threatening. Call your healthcare provider right away if you have any of these symptoms:

- yellowing of your skin or the whites of your eyes (jaundice)
- dark urine
- nausea or vomiting
- loss of appetite
- pain on the right side of your stomach (abdomen)

3. Like other antiepileptic drugs, FELBATOL may cause suicidal thoughts or actions in a very small number of people, about 1 in 500.

Call your healthcare provider right away if you have any of these symptoms, especially if they are new, worse, or worry you:

- thoughts about suicide or dying
- new or worse depression
- attempts to commit suicide
- feeling agitated or restless
- new or worse anxiety
- trouble sleeping (insomnia)
- panic attacks
- acting aggressive, being angry, or violent
- new or worse irritability
- acting on dangerous impulses
- an extreme increase in activity and talking (mania)
- other unusual changes in behavior or mood

How can I watch for early symptoms of suicidal thoughts and actions?

- Pay attention to any changes, especially sudden changes, in mood, behaviors, thoughts, or feelings.
- Keep all follow-up visits with your healthcare provider as scheduled.

Call your healthcare provider between visits as needed, especially if you are worried about symptoms.

Do not stop FELBATOL without first talking to a healthcare provider.

Stopping FELBATOL suddenly can cause serious problems. You should talk to your healthcare provider before stopping. Stopping a seizure medicine suddenly in a patient who has epilepsy can cause seizures.

Suicidal thoughts or actions can be caused by things other than medicines. If you have suicidal thoughts or actions, your healthcare provider may check for other causes.

What is FELBATOL?

FELBATOL is a prescription medicine used when other treatments have failed in:

- adults alone or with other medicines to treat:
  - partial seizures with and without generalization
- children with other medicines to treat:
  - seizures associated with Lennox-Gastaut syndrome

Who should not take FELBATOL?

Do not take FELBATOL if you:

- are allergic to felbamate, carbamates or any of the ingredients in FELBATOL.

See the end of this Medication Guide for a complete list of ingredients in FELBATOL.

- have or have had blood problems
- have or have had liver problems

What should I tell my healthcare provider before taking FELBATOL?

Before you take FELBATOL, tell your healthcare provider if you:

- have kidney problems
- have or have had depression, mood problems, or suicidal thoughts or behavior
- have any other medical conditions
- are pregnant or plan to become pregnant. It is not known if FELBATOL can harm your unborn baby. Tell your healthcare provider right away if you become pregnant while taking FELBATOL. You and your healthcare provider will decide if you should take FELBATOL while you are pregnant.
  - If you become pregnant while taking FELBATOL, talk to your healthcare provider about registering with the North American Antiepileptic Drug (NAAED) Pregnancy Registry. The purpose of this registry is to collect information about the safety of antiepileptic medicine during pregnancy. You can enroll in this registry by calling 1-888-233-2334.
- are breastfeeding or plan to breastfeed. FELBATOL may pass into your breast milk. You and your healthcare provider should decide if you should take FELBATOL while you breastfeed.

Tell your healthcare provider about all the medicines you take, including prescription and non-prescription medicines, vitamins, and herbal supplements.

Taking FELBATOL with certain other medicines can cause side effects or affect how well they work. Do not start or stop other medicines without talking to your healthcare provider.

Know the medicines you take. Keep a list of them and show it to your healthcare provider and pharmacist when you get a new medicine.

How should I take FELBATOL?

- Take FELBATOL exactly as your healthcare provider tells you. Your healthcare provider will tell you how much FELBATOL to take and when to take it.
- Your healthcare provider may change your dose of FELBATOL. Do not change your dose of FELBATOL without talking to your healthcare provider.
- Because of the risk of serious blood and liver problems, your healthcare provider may do blood tests before you start and while you take FELBATOL.
- If you take too much FELBATOL, call your healthcare provider or local Poison Control Center right away.
- Do not stop FELBATOL without first talking to your healthcare provider.

What should I avoid while taking FELBATOL?

- FELBATOL can cause drowsiness and dizziness. Do not drink alcohol or take other medicines that make you sleepy or dizzy while taking FELBATOL, until you talk with your doctor. Taking FELBATOL with alcohol or drugs that cause sleepiness or dizziness may make your sleepiness or dizziness worse.

What are the possible side effects of FELBATOL?

See “What is the most important information I should know about FELBATOL?”

FELBATOL may cause serious side effects including:

The most common side effects of FELBATOL include:

- weight loss
- trouble sleeping
- sleepiness
- vomiting
- nausea
- headache
- changes in the way that food tastes
- dizziness
- double-vision

These are not all the possible side effects of FELBATOL. For more information, ask your healthcare provider or pharmacist.

Tell your healthcare provider if you have any side effect that bothers you or that does not go away.

Call your doctor for medical advice about side effects. You may report side effects to FDA at 1-800-FDA-1088.

How should I store FELBATOL?

- Store FELBATOL at room temperature between 68°F to 77°F (20°C to 25°C).

Keep FELBATOL and all medicines out of the reach of children.

General information about FELBATOL.

Medicines are sometimes prescribed for purposes other than those listed in a Medication Guide. Do not use FELBATOL for a condition for which it was not prescribed. Do not give FELBATOL to other people, even if they have the same symptoms that you have. It may harm them.

This Medication Guide summarizes the most important information about FELBATOL. If you would like more information, talk with your healthcare provider. You can ask your pharmacist or healthcare provider for information about FELBATOL that is written for health professionals.

What are the ingredients in FELBATOL?

Active Ingredient: felbamate

Tablet Inactive Ingredients: starch, microcrystalline cellulose, croscarmellose sodium, lactose, magnesium stearate, FD&C Yellow No. 6, D&C Yellow No. 10, and FD&C Red No. 40 (600 mg tablets only).

Suspension Inactive Ingredients: sorbitol, glycerin, microcrystalline cellulose, carboxymethylcellulose sodium, simethicone, polysorbate 80, methylparaben, saccharin sodium, propylparaben, FD&C Yellow No. 6, FD&C Red No. 40, flavorings, and purified water.

For more information, call Viatris at 1-877-446-3679 (1-877-4-INFO-RX).

FELBATOL is a registered trademark of Meda Pharmaceuticals Inc., a Viatris Company.

© 2025 Viatris Inc.

Distributed by:
Viatris Specialty LLC
Morgantown, WV 26505 U.S.A.

This Medication Guide has been approved by the U.S. Food and Drug Administration.

Rx Only
Revised: 8/2025

VS:SOV:MG:FELT:R1m

PRINCIPAL DISPLAY PANEL – 100 count Bottle, 400 mg Tablet

NDC 0037-0430-01

100 Tablets

Felbatol®
(felbamate)

Tablets 400 mg

Rx only

FELBATOL is a registered trademark of
Meda Pharmaceuticals Inc., a Viatris Company.

© 2025 Viatris Inc.

Usual Dosage: For full prescribing
information, see accompanying
package insert.

Store at controlled room temperature
20°-25°C (68°-77°F).

Dispense the accompanying
Medication Guide to each patient.

Dispense in a tight container.

Distributed by:
Viatris Specialty LLC
Morgantown, WV 26505 U.S.A.

VSSOV0430A1
200992-01

Rev. 8/2025

PRINCIPAL DISPLAY PANEL – 100 count Bottle, 600 mg Tablet

NDC 0037-0431-01

100 Tablets

Felbatol®
(felbamate)

Tablets 600 mg

Rx only

FELBATOL is a registered trademark of
Meda Pharmaceuticals Inc., a Viatris Company.

© 2025 Viatris Inc.

Usual Dosage: For full prescribing
information, see accompanying
package insert.

Store at controlled room temperature
20°-25°C (68°-77°F).

Dispense the accompanying
Medication Guide to each patient.

Dispense in a tight container.

Distributed by:
Viatris Specialty LLC
Morgantown, WV 26505 U.S.A.

VSSOV0431A1
200993-01

Rev. 8/2025

PRINCIPAL DISPLAY PANEL – 8 fl oz (237 mL) Bottle, 600 mg Suspension

NDC 0037-0442-67

8 fl oz (237 mL)

Felbatol®
(felbamate)
Oral Suspension

Each 5 mL contains
600 mg felbamate

Rx Only

SHAKE WELL

MEDA
PHARMACEUTICALS®

LB-024F5-12 141232-0821

Usual Dosage: For full prescribing information, see
accompanying package insert.

Store at controlled room temperature 20°-25°C (68°-77°F).

Dispense the accompanying Medication Guide to each
patient.

Dispense in a tight container.

Manufactured for:
Meda Pharmaceuticals Inc.
Somerset, New Jersey 08873-4120